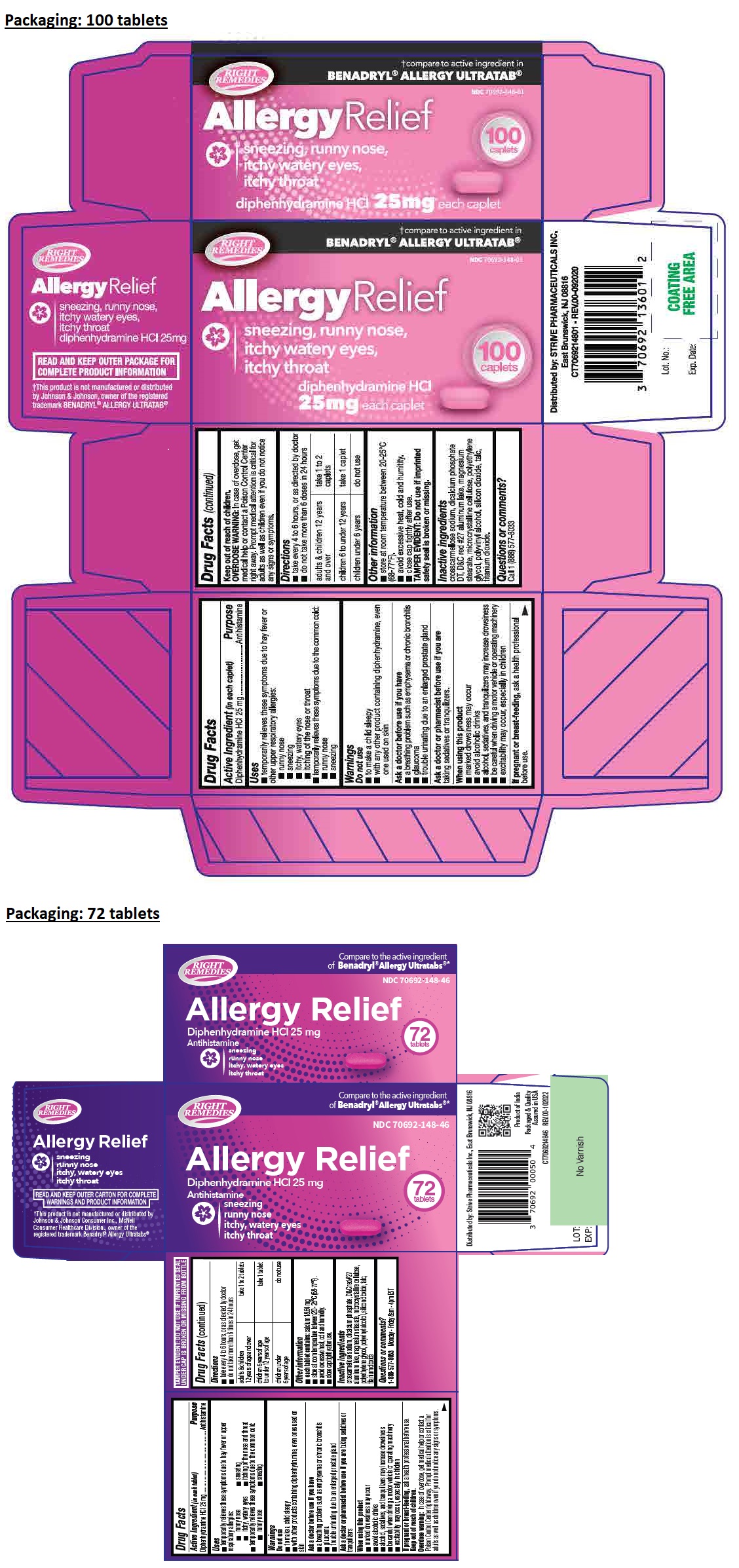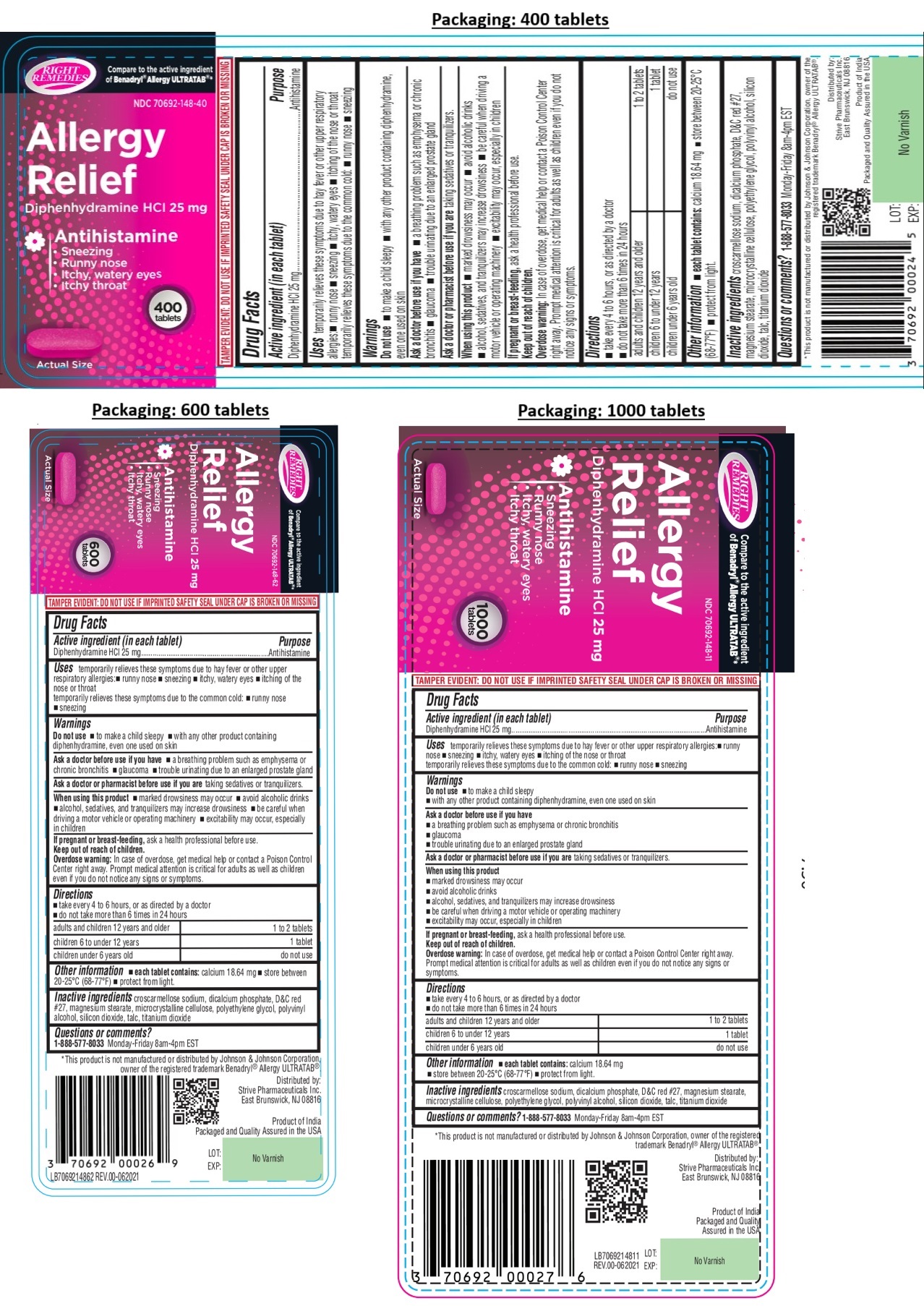 DRUG LABEL: Diphenhydramine Hydrochloride 25mg
NDC: 70692-148 | Form: TABLET
Manufacturer: Strive Pharmaceuticals Inc
Category: otc | Type: HUMAN OTC DRUG LABEL
Date: 20241211

ACTIVE INGREDIENTS: DIPHENHYDRAMINE HYDROCHLORIDE 25 mg/1 1
INACTIVE INGREDIENTS: CROSCARMELLOSE SODIUM; POLYVINYL ALCOHOL, UNSPECIFIED; TALC; POLYETHYLENE GLYCOL, UNSPECIFIED; MAGNESIUM STEARATE; TITANIUM DIOXIDE; SILICON DIOXIDE; MICROCRYSTALLINE CELLULOSE; D&C RED NO. 27; ANHYDROUS DIBASIC CALCIUM PHOSPHATE

RIGHT REMEDIES Allergy Relief

Active ingredient (in each tablet)

Diphenhydramine HCl 25 mg

Purpose

Antihistamine

Uses

temporarily relieves these symptoms due to hay fever or upper respiratory allergies:
• runny nose • sneezing
• itchy, watery eyes • itching of the nose or throat
temporarily relieves these symptoms due to the common cold:
• runny nose • sneezing

Warnings

Do not use
• to make a child sleepy
• with any other product containing diphenhydramine, even one used on skin

Ask a doctor before use if you have
• a breathing problem such as emphysema or chronic bronchitis
• glaucoma
• trouble urinating due to an enlarged prostate gland

Ask a doctor or pharmacist before use if you are taking sedatives or tranquilizers.

When using this product
• marked drowsiness may occur
• avoid alcoholic drinks
• alcohol, sedatives, and tranquilizers may increase drowsiness
• be careful when driving a motor vehicle or operating machinery
• excitability may occur, especially in children

If pregnant or breast-feeding, ask a health professional before use.

Keep out of reach of children.
Overdose warning: In case of overdose, get medical help or contact a Poison Control Center right away. Prompt medical attention is critical for adults as well as children even if you do not notice any signs or symptoms.

Directions

• take every 4 to 6 hours, or as directed by doctor
• do not take more than 6 times in 24 hours

adults and children 12 years and older | 1 to 2 tablets
children 6 to under 12 years | 1 tablet
children under 6 years old | do not use

Other information

• each tablet contains: calcium 18.64 mg
• store between 20-25°C (68-77°F)
• protect from light.

Inactive ingredients

croscarmellose sodium, dicalcium phosphate, D&C red #27, magnesium stearate, microcrystalline cellulose, polyethylene glycol, polyvinyl alcohol, silicon dioxide, talc, titanium dioxide

Questions or comments?

1-888-577-8033 Monday-Friday 8am-4pm EST

RIGHT REMEDIES

Compare to the active ingredient of Benadryl® Allergy ULTRATAB®*

*This product is not manufactured or distributed by Johnson & Johnson Corporation, owner of the registered trademark Benadryl® Allergy ULTRATAB®

Distributed by:
Strive Pharmaceuticals Inc.
East Brunswick, NJ 08816

Product of India
Packaged and Quality Assured in the USA

TAMPER EVIDENT: DO NOT USE IF IMPRINTED SAFETY SEAL UNDER CAP IS BROKEN OR MISSING